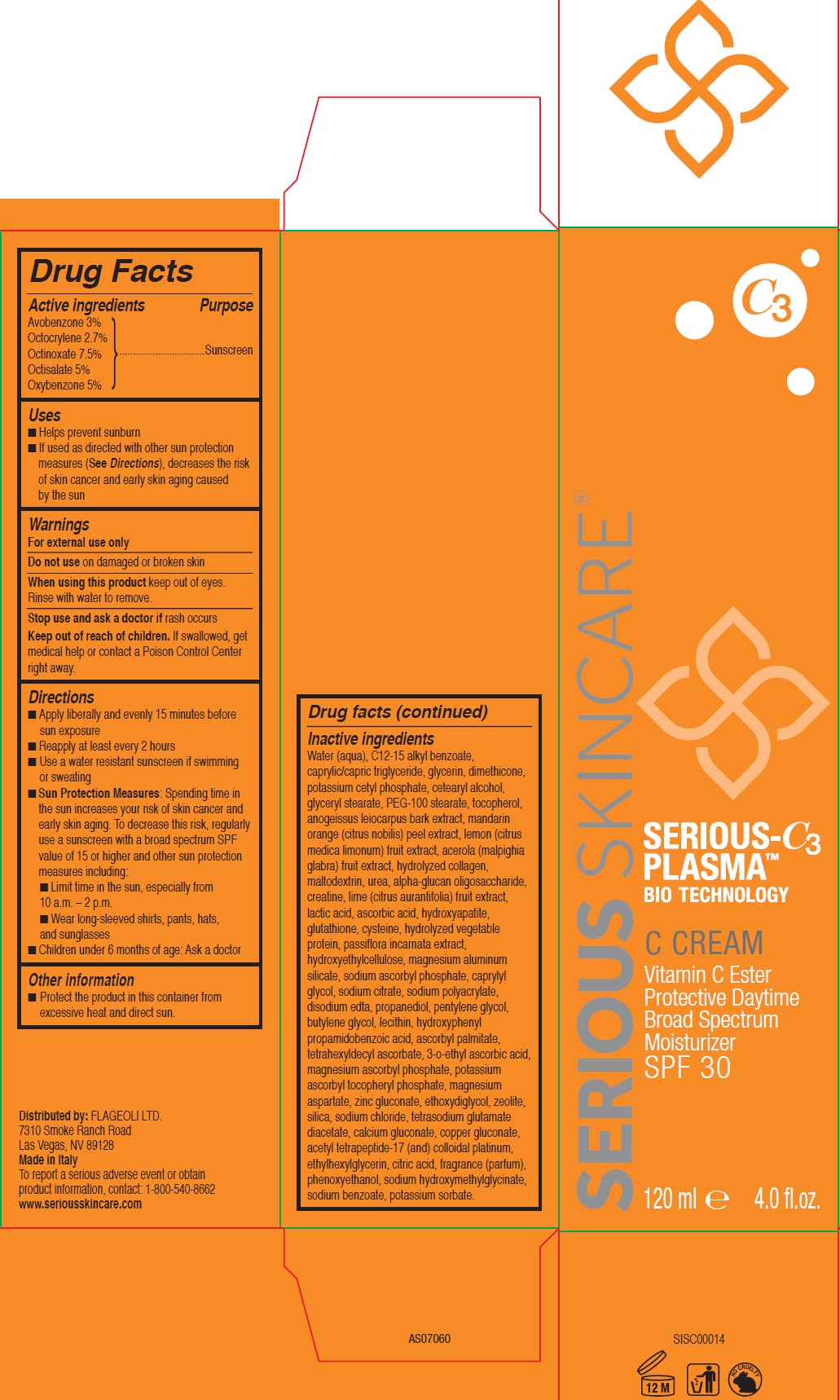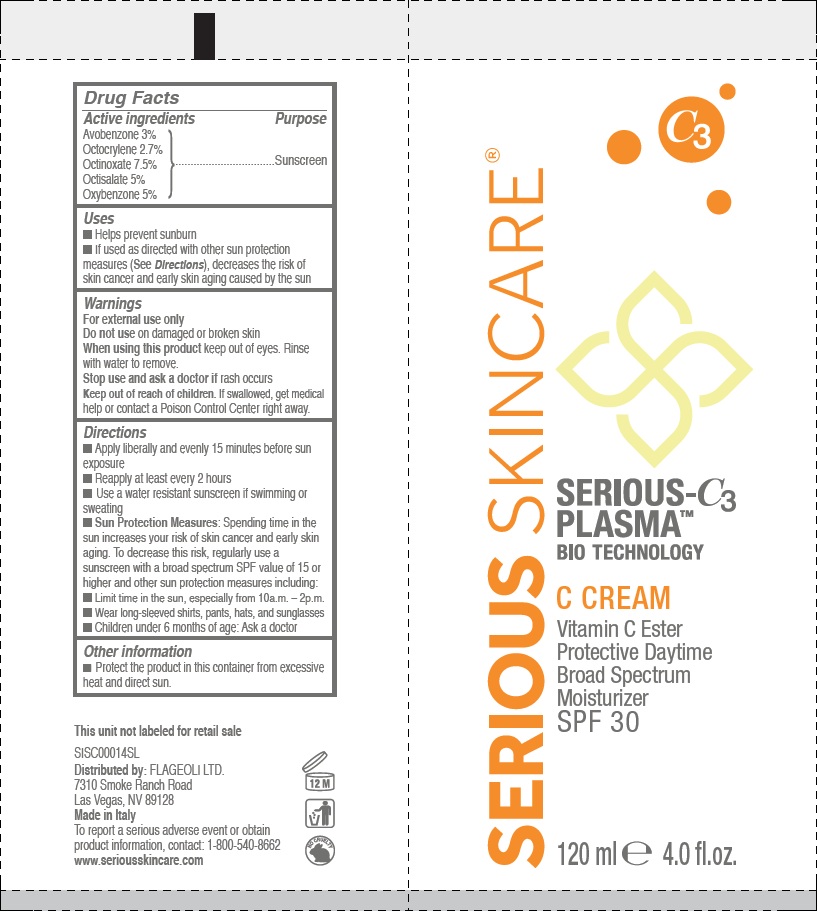 DRUG LABEL: SERIOUS SKINCARE SERIOUS C3 PLASMA BIO TECHNOLOGY C VITAMIN C ESTER PROTECTIVE DAYTIME BROAD SPECTRUM MOISTURIZER SPF 30
NDC: 53755-101 | Form: CREAM
Manufacturer: Flageoli Limited
Category: otc | Type: HUMAN OTC DRUG LABEL
Date: 20231212

ACTIVE INGREDIENTS: AVOBENZONE 30 mg/1 mL; OCTOCRYLENE 27 mg/1 mL; OCTINOXATE 75 mg/1 mL; OCTISALATE 50 mg/1 mL; OXYBENZONE 50 mg/1 mL
INACTIVE INGREDIENTS: LIME (CITRUS); LACTIC ACID; ASCORBIC ACID; TRIBASIC CALCIUM PHOSPHATE; GLUTATHIONE; CYSTEINE; MAGNESIUM ALUMINUM SILICATE; SODIUM ASCORBYL PHOSPHATE; CAPRYLYL GLYCOL; SODIUM CITRATE; EDETATE DISODIUM ANHYDROUS; PROPANEDIOL; PENTYLENE GLYCOL; BUTYLENE GLYCOL; HYDROXYPHENYL PROPAMIDOBENZOIC ACID; ASCORBYL PALMITATE; TETRAHEXYLDECYL ASCORBATE; 3-O-ETHYL ASCORBIC ACID; MAGNESIUM ASCORBYL PHOSPHATE; POTASSIUM ASCORBYL TOCOPHERYL PHOSPHATE; MAGNESIUM ASPARTATE; ZINC GLUCONATE; DIETHYLENE GLYCOL MONOETHYL ETHER; SILICON DIOXIDE; SODIUM CHLORIDE; TETRASODIUM GLUTAMATE DIACETATE; CALCIUM GLUCONATE; COPPER GLUCONATE; ETHYLHEXYLGLYCERIN; CITRIC ACID MONOHYDRATE; PHENOXYETHANOL; SODIUM HYDROXYMETHYLGLYCINATE; SODIUM BENZOATE; POTASSIUM SORBATE; WATER; ALKYL (C12-15) BENZOATE; MEDIUM-CHAIN TRIGLYCERIDES; GLYCERIN; DIMETHICONE; POTASSIUM CETYL PHOSPHATE; CETOSTEARYL ALCOHOL; GLYCERYL MONOSTEARATE; PEG-100 STEARATE; TOCOPHEROL; ANOGEISSUS LEIOCARPUS BARK; CITRUS NOBILIS; MALTODEXTRIN; UREA; CREATINE; .ALPHA.-GLUCAN OLIGOSACCHARIDE

SERIOUS SKINCARE SERIOUS-C3 PLASMA BIO TECHNOLOGY C CREAM VITAMIN C ESTER PROTECTIVE DAYTIME BROAD SPECTRUM MOISTURIZER SPF 30

Active ingredients

Avobenzone 3% Octocrylene 2.7% Octinoxate 7.5% Octisalate 5% Oxybenzone 5%

Purpose

Sunscreen

Uses

- Helps prevent sunburn
- If used as directed with other sun protection measures (), decreases the risk of skin cancer and early skin aging caused by the sun See Directions

Warnings

For external use only

Do not use on

damaged or broken skin

When using this product

keep out of eyes. Rinse with water to remove.

Stop use and ask a doctor if

rash occurs

Keep out of reach of children.

If swallowed, get medical help or contact a Poison Control Center right away.

Directions

- Apply liberally and evenly 15 minutes before sun exposure
- Reapply at least every 2 hours
- Use a water resistant sunscreen if swimming or sweating
- Spending time in the sun increases your risk of skin cancer and early skin aging. To decrease this risk, regularly use a sunscreen with a broad spectrum SPF value of 15 or higher and other sun protection measures including: Sun Protection Measures:
- Limit time in the sun, especially from 10 a.m. – 2 p.m.
- Wear long-sleeved shirts, pants, hats, and sunglasses
- Children under 6 months of age: Ask a doctor

Other information

Protect the product in this container from excessive heat and direct sun.

Inactive ingredients

Water (aqua), C12-15 alkyl benzoate, caprylic/capric triglyceride, glycerin, dimethicone, potassium cetyl phosphate, cetearyl alcohol, glyceryl stearate, PEG-100 stearate, tocopherol, anogeissus leiocarpus bark extract, mandarin orange (citrus nobilis) peel extract, lemon (citrus medica limonum) fruit extract, acerola (malpighia glabra) fruit extract, hydrolyzed collagen, maltodextrin, urea, alpha-glucan oligosaccharide, creatine, lime (citrus aurantifolia) fruit extract, lactic acid, ascorbic acid, hydroxyapatite, glutathione, cysteine, hydrolyzed vegetable protein, passiflora incarnata extract, hydroxyethylcellulose, magnesium aluminum silicate, sodium ascorbyl phosphate, caprylyl�glycol, sodium citrate, sodium polyacrylate, disodium edta, propanediol, pentylene glycol, butylene glycol, lecithin, hydroxyphenyl propamidobenzoic acid, ascorbyl palmitate, tetrahexyldecyl ascorbate, 3-o-ethyl ascorbic acid, magnesium ascorbyl phosphate, potassium ascorbyl tocopheryl phosphate, magnesium aspartate, zinc gluconate, ethoxydiglycol, zeolite, silica, sodium chloride, tetrasodium glutamate diacetate, calcium gluconate, copper gluconate, acetyl tetrapeptide-17 (and) colloidal platinum, ethylhexylglycerin, citric acid, fragrance (parfum), phenoxyethanol, sodium hydroxymethylglycinate, sodium benzoate, potassium sorbate.